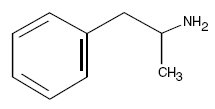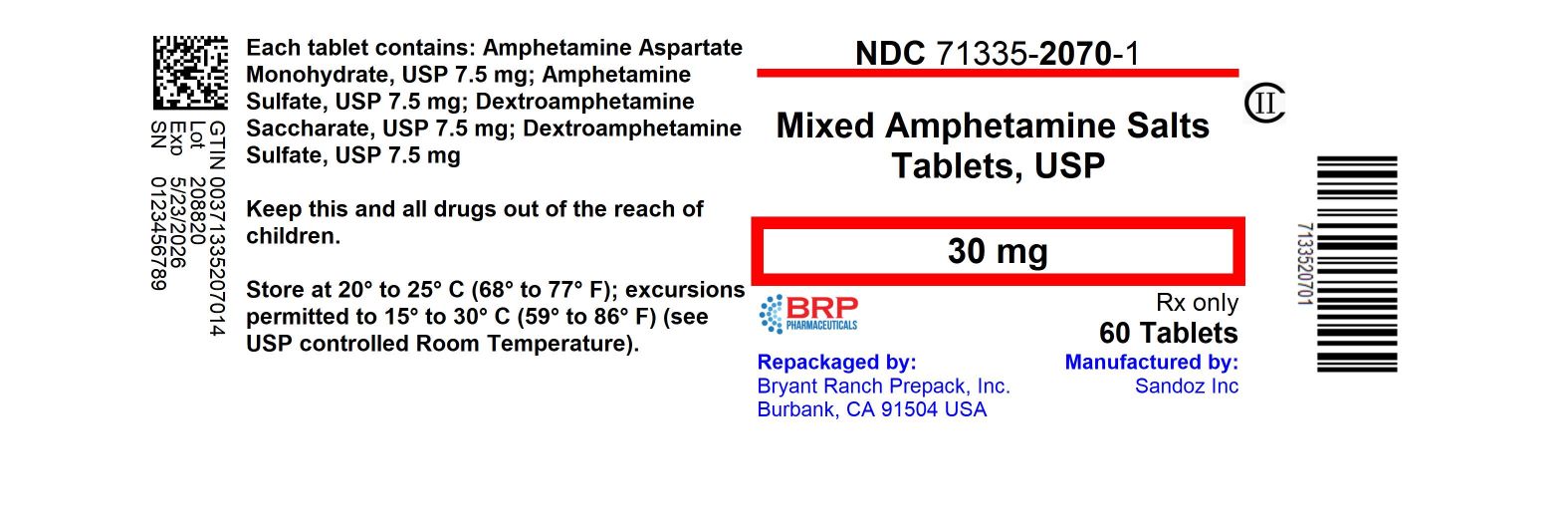 DRUG LABEL: Dextroamphetamine Saccharate, Amphetamine Aspartate Monohydrate, Dextroamphetamine Sulfate and Amphetamine Sulfate
NDC: 71335-2070 | Form: TABLET
Manufacturer: Bryant Ranch Prepack
Category: prescription | Type: HUMAN PRESCRIPTION DRUG LABEL
Date: 20240523
DEA Schedule: CII

ACTIVE INGREDIENTS: DEXTROAMPHETAMINE SACCHARATE 7.5 mg/1 1; AMPHETAMINE ASPARTATE MONOHYDRATE 7.5 mg/1 1; DEXTROAMPHETAMINE SULFATE 7.5 mg/1 1; AMPHETAMINE SULFATE 7.5 mg/1 1
INACTIVE INGREDIENTS: FD&C YELLOW NO. 6; LACTOSE MONOHYDRATE; MAGNESIUM STEARATE; STARCH, CORN

Dextroamphetamine Saccharate, Amphetamine Aspartate, Dextroamphetamine Sulfate and Amphetamine Sulfate Tablets CII
(Mixed Salts of a Single Entity Amphetamine Product)

BOXED WARNING

AMPHETAMINES HAVE A HIGH POTENTIAL FOR ABUSE. ADMINISTRATION OF AMPHETAMINES FOR PROLONGED PERIODS OF TIME MAY LEAD TO DRUG DEPENDENCE AND MUST BE AVOIDED. PARTICULAR ATTENTION SHOULD BE PAID TO THE POSSIBILITY OF SUBJECTS OBTAINING AMPHETAMINES FOR NON-THERAPEUTIC USE OR DISTRIBUTION TO OTHERS, AND THE DRUGS SHOULD BE PRESCRIBED OR DISPENSED SPARINGLY.

MISUSE OF AMPHETAMINE MAY CAUSE SUDDEN DEATH AND SERIOUS CARDIOVASCULAR ADVERSE EVENTS.

DESCRIPTION

A single-entity amphetamine product combining the neutral sulfate salts of dextroamphetamine and amphetamine, with the dextro isomer of amphetamine saccharate and d, l-amphetamine aspartate monohydrate.

The structural formula is:

C9H13N MW=135.21

Each Tablet Contains

 | 5 mg | 10 mg | 20 mg | 30 mg
Dextroamphetamine Saccharate | 1.25 mg | 2.5 mg | 5 mg | 7.5 mg
Amphetamine Aspartate Monohydrate | 1.25 mg | 2.5 mg | 5 mg | 7.5 mg
Dextroamphetamine Sulfate USP | 1.25 mg | 2.5 mg | 5 mg | 7.5 mg
Amphetamine Sulfate USP | 1.25 mg | 2.5 mg | 5 mg | 7.5 mg
Total amphetamine base equivalence | 3.13 mg | 6.3 mg | 12.6 mg | 18.8 mg

In addition each tablet for oral administration contains the following inactive ingredients: lactose monohydrate, pregelatinized starch (corn) and magnesium stearate.

In addition dextroamphetamine saccharate, amphetamine aspartate, dextroamphetamine sulfate and amphetamine sulfate tablets (mixed salts of a single entity amphetamine product) 5 mg and 10 mg contain FD&C blue No. 1 aluminum lake and the 20 mg and 30 mg contain FD&C yellow No. 6 aluminum lake as color additives.

CLINICAL PHARMACOLOGY

Pharmacodynamics

Amphetamines are non-catecholamine sympathomimetic amines with CNS stimulant activity. The mode of therapeutic action in attention deficit hyperactivity disorder (ADHD) is not known. Amphetamines are thought to block the reuptake of norepinephrine and dopamine into the presynaptic neuron and increase the release of these monoamines into the extraneuronal space.

Pharmacokinetics

Mixed salts of a single entity amphetamine product contain d-amphetamine and l-amphetamine salts in the ratio of 3:1. Following administration of a single dose 10 mg or 30 mg of mixed salts of a single entity amphetamine product to healthy volunteers under fasted conditions, peak plasma concentrations occurred approximately 3 hours post-dose for both d-amphetamine and l-amphetamine. The mean elimination half-life (t½) for d-amphetamine was shorter than the t½ of the l-isomer (9.77 to 11 hours vs. 11.5 to 13.8 hours). The PK parameters (Cmax, AUC0-inf) of d-and l-amphetamine increased approximately three-fold from 10 mg to 30 mg indicating dose-proportional pharmacokinetics.

The effect of food on the bioavailability of mixed salts of a single entity amphetamine product has not been studied.

Metabolism and Excretion

Amphetamine is reported to be oxidized at the 4 position of the benzene ring to form 4-hydroxyamphetamine, or on the side chain α or β carbons to form alpha-hydroxy-amphetamine or norephedrine, respectively. Norephedrine and 4-hydroxy-amphetamine are both active and each is subsequently oxidized to form 4-hydroxy-norephedrine. Alpha-hydroxy-amphetamine undergoes deamination to form phenylacetone, which ultimately forms benzoic acid and its glucuronide and the glycine conjugate hippuric acid. Although the enzymes involved in amphetamine metabolism have not been clearly defined, CYP2D6 is known to be involved with formation of 4-hydroxy-amphetamine. Since CYP2D6 is genetically polymorphic, population variations in amphetamine metabolism are a possibility.

Amphetamine is known to inhibit monoamine oxidase, whereas the ability of amphetamine and its metabolites to inhibit various P450 isozymes and other enzymes has not been adequately elucidated. In vitro experiments with human microsomes indicate minor inhibition of CYP2D6 by amphetamine and minor inhibition of CYP1A2, 2D6, and 3A4 by one or more metabolites. However, due to the probability of auto-inhibition and the lack of information on the concentration of these metabolites relative to in vivo concentrations, no predications regarding the potential for amphetamine or its metabolites to inhibit the metabolism of other drugs by CYP isozymes in vivo can be made.

With normal urine pHs approximately half of an administered dose of amphetamine is recoverable in urine as derivatives of alpha-hydroxy-amphetamine and approximately another 30% to 40% of the dose is recoverable in urine as amphetamine itself. Since amphetamine has a pKa of 9.9, urinary recovery of amphetamine is highly dependent on pH and urine flow rates. Alkaline urine pHs result in less ionization and reduced renal elimination, and acidic pHs and high flow rates result in increased renal elimination with clearances greater than glomerular filtration rates, indicating the involvement of active secretion. Urinary recovery of amphetamine has been reported to range from 1% to 75%, depending on urinary pH, with the remaining fraction of the dose hepatically metabolized. Consequently, both hepatic and renal dysfunction have the potential to inhibit the elimination of amphetamine and result in prolonged exposures. In addition, drugs that affect urinary pH are known to alter the elimination of amphetamine, and any decrease in amphetamine’s metabolism that might occur due to drug interactions or genetic polymorphisms is more likely to be clinically significant when renal elimination is decreased (see PRECAUTIONS).

INDICATIONS AND USAGE

Mixed salts of a single entity amphetamine product are indicated for the treatment of attention deficit hyperactivity disorder (ADHD) and narcolepsy.

Attention Deficit Hyperactivity Disorder (ADHD)

A diagnosis of attention deficit hyperactivity disorder (ADHD; DSM-IV®) implies the presence of hyperactive-impulsive or inattentive symptoms that caused impairment and were present before age 7 years. The symptoms must cause clinically significant impairment, e.g., in social, academic, or occupational functioning, and be present in two or more settings, e.g., school (or work) and at home. The symptoms must not be better accounted for by another mental disorder. For the Inattentive Type, at least six of the following symptoms must have persisted for at least 6 months: lack of attention to details/careless mistakes; lack of sustained attention; poor listener; failure to follow through on tasks; poor organization; avoids tasks requiring sustained mental effort; loses things; easily distracted; forgetful. For the Hyperactive-Impulsive Type, at least six of the following symptoms must have persisted for at least 6 months: fidgeting/squirming; leaving seat; inappropriate running/climbing; difficulty with quiet activities; "on the go;" excessive talking; blurting answers; can't wait turn; intrusive. The combined type requires both inattentive and hyperactive-impulsive criteria to be met.

Special Diagnostic Considerations

Specific etiology of this syndrome is unknown, and there is no single diagnostic test. Adequate diagnosis requires the use not only of medical but of special psychological, educational, and social resources. Learning may or may not be impaired. The diagnosis must be based upon a complete history and evaluation of the child and not solely on the presence of the required number of DSM-IV® characteristics.

Need for Comprehensive Treatment Program

Mixed salts of a single entity amphetamine product are indicated as an integral part of a total treatment program for ADHD that may include other measures (psychological, educational, social) for patients with this syndrome. Drug treatment may not be indicated for all children with this syndrome. Stimulants are not intended for use in the child who exhibits symptoms secondary to environmental factors and/or other primary psychiatric disorders, including psychosis. Appropriate educational placement is essential and psychosocial intervention is often helpful. When remedial measures alone are insufficient, the decision to prescribe stimulant medication will depend upon the physician's assessment of the chronicity and severity of the child's symptoms.

Long-Term Use

The effectiveness of mixed salts of a single entity amphetamine product for long-term use has not been systematically evaluated in controlled trials. Therefore, the physician who elects to use mixed salts of a single entity amphetamine product for extended periods should periodically re-evaluate the long-term usefulness of the drug for the individual patient.

CONTRAINDICATIONS

Advanced arteriosclerosis, symptomatic cardiovascular disease, moderate to severe hypertension, hyperthyroidism, known hypersensitivity or idiosyncrasy to the sympathomimetic amines, glaucoma.

Agitated states.

Known hypersensitivity or idiosyncrasy to amphetamine.

Patients with a history of drug abuse.

In patients known to be hypersensitive to amphetamine, or other components of mixed salts of a single entity amphetamine product. Hypersensitivity reactions such as angioedema and anaphylactic reactions have been reported in patients treated with other amphetamine products (see ADVERSE REACTIONS).

Patients taking monoamine oxidase inhibitors (MAOIs), or within 14 days of stopping MAOIs (including MAOIs such as linezolid or intravenous methylene blue), because of an increased risk of hypertensive crisis (see WARNINGS and Drug Interactions).

WARNINGS

Serious Cardiovascular Events

Sudden Death and Preexisting Structural Cardiac

Abnormalities or Other Serious Heart Problems

Children and Adolescents

Sudden death has been reported in association with CNS stimulant treatment at usual doses in children and adolescents with structural cardiac abnormalities or other serious heart problems. Although some structural heart problems alone may carry an increased risk of sudden death, stimulant products generally should not be used in children or adolescents with known structural cardiac abnormalities, cardiomyopathy, serious heart rhythm abnormalities, or other serious cardiac problems that may place them at increased vulnerability to the sympathomimetic effects of a stimulant drug (see CONTRAINDICATIONS).

Adults

Sudden deaths, stroke, and myocardial infarction have been reported in adults taking stimulant drugs at usual doses for ADHD. Although the role of stimulants in these adult cases is also unknown, adults have a greater likelihood than children of having serious structural cardiac abnormalities, cardiomyopathy, serious heart rhythm abnormalities, coronary artery disease, or other serious cardiac problems. Adults with such abnormalities should also generally not be treated with stimulant drugs (see CONTRAINDICATIONS).

Hypertension and Other Cardiovascular Conditions

Stimulant medications cause a modest increase in average blood pressure (about 2 mmHg to 4 mmHg) and average heart rate (about 3 bpm to 6 bpm) (see ADVERSE REACTIONS), and individuals may have larger increases. While the mean changes alone would not be expected to have short-term consequences, all patients should be monitored for larger changes in heart rate and blood pressure. Caution is indicated in treating patients whose underlying medical conditions might be compromised by increases in blood pressure or heart rate, e.g., those with preexisting hypertension, heart failure, recent myocardial infarction, or ventricular arrhythmia (see CONTRAINDICATIONS).

Assessing Cardiovascular Status in Patients Being Treated With Stimulant Medications

Children, adolescents, or adults who are being considered for treatment with stimulant medications should have a careful history (including assessment for a family history of sudden death or ventricular arrhythmia) and physical exam to assess for the presence of cardiac disease, and should receive further cardiac evaluation if findings suggest such disease (e.g., electrocardiogram and echocardiogram). Patients who develop symptoms such as exertional chest pain, unexplained syncope, or other symptoms suggestive of cardiac disease during stimulant treatment should undergo a prompt cardiac evaluation.

Psychiatric Adverse Events

Preexisting Psychosis

Administration of stimulants may exacerbate symptoms of behavior disturbance and thought disorder in patients with preexisting psychotic disorder.

Bipolar Illness

Particular care should be taken in using stimulants to treat ADHD patients with comorbid bipolar disorder because of concern for possible induction of mixed/manic episode in such patients. Prior to initiating treatment with a stimulant, patients with comorbid depressive symptoms should be adequately screened to determine if they are at risk for bipolar disorder; such screening should include a detailed psychiatric history, including a family history of suicide, bipolar disorder, and depression.

Emergence of New Psychotic or Manic Symptoms

Treatment emergent psychotic or manic symptoms, e.g., hallucinations, delusional thinking, or mania in children and adolescents without prior history of psychotic illness or mania can be caused by stimulants at usual doses. If such symptoms occur, consideration should be given to a possible causal role of the stimulant, and discontinuation of treatment may be appropriate. In a pooled analysis of multiple short-term, placebo-controlled studies, such symptoms occurred in about 0.1% (4 patients with events out of 3,482 exposed to methylphenidate or amphetamine for several weeks at usual doses) of stimulant-treated patients compared to 0 in placebo-treated patients.

Aggression

Aggressive behavior or hostility is often observed in children and adolescents with ADHD, and has been reported in clinical trials and the postmarketing experience of some medications indicated for the treatment of ADHD. Although there is no systematic evidence that stimulants cause aggressive behavior or hostility, patients beginning treatment for ADHD should be monitored for the appearance of or worsening of aggressive behavior or hostility.

Long-Term Suppression of Growth

Careful follow-up of weight and height in children ages 7 to 10 years who were randomized to either methylphenidate or non-medication treatment groups over 14 months, as well as in naturalistic subgroups of newly methylphenidate-treated and non-medication treated children over 36 months (to the ages of 10 to 13 years), suggests that consistently medicated children (i.e., treatment for 7 days per week throughout the year) have a temporary slowing in growth rate (on average, a total of about 2 cm less growth in height and 2.7 kg less growth in weight over 3 years), without evidence of growth rebound during this period of development.

Published data are inadequate to determine whether chronic use of amphetamines may cause a similar suppression of growth, however, it is anticipated that they will likely have this effect as well. Therefore, growth should be monitored during treatment with stimulants, and patients who are not growing or gaining weight as expected may need to have their treatment interrupted.

Seizures

There is some clinical evidence that stimulants may lower the convulsive threshold in patients with prior history of seizure, in patients with prior EEG abnormalities in absence of seizures, and very rarely, in patients without a history of seizures and no prior EEG evidence of seizures. In the presence of seizures, the drug should be discontinued.

Peripheral Vasculopathy, Including Raynaud’s Phenomenon

Stimulants, including mixed salts of a single entity amphetamine product, used to treat ADHD are associated with peripheral vasculopathy, including Raynaud’s phenomenon. Signs and symptoms are usually intermittent and mild; however, very rare sequelae include digital ulceration and/or soft tissue breakdown. Effects of peripheral vasculopathy, including Raynaud’s phenomenon, were observed in postmarketing reports at different times and at therapeutic doses in all age groups throughout the course of treatment. Signs and symptoms generally improve after reduction in dose or discontinuation of drug. Careful observation for digital changes is necessary during treatment with ADHD stimulants. Further clinical evaluation (e.g., rheumatology referral) may be appropriate for certain patients.

Serotonin Syndrome

Serotonin syndrome, a potentially life-threatening reaction, may occur when amphetamines are used in combination with other drugs that affect the serotonergic neurotransmitter systems such as monoamine oxidase inhibitors (MAOIs), selective serotonin reuptake inhibitors (SSRIs), serotonin norepinephrine reuptake inhibitors (SNRIs), triptans, tricyclic antidepressants, fentanyl, lithium, tramadol, tryptophan, buspirone, and St. John’s Wort (see Drug Interactions). Amphetamines and amphetamine derivatives are known to be metabolized, to some degree, by cytochrome P450 2D6 (CYP2D6) and display minor inhibition of CYP2D6 metabolism (see CLINICAL PHARMACOLOGY). The potential for a pharmacokinetic interaction exists with the co-administration of CYP2D6 inhibitors which may increase the risk with increased exposure to dextroamphetamine saccharate, amphetamine aspartate, dextroamphetamine sulfate, amphetamine sulfate. In these situations, consider an alternative non-serotonergic drug or an alternative drug that does not inhibit CYP2D6 (see Drug Interactions).

Serotonin syndrome symptoms may include mental status changes (e.g., agitation, hallucinations, delirium, and coma), autonomic instability (e.g., tachycardia, labile blood pressure, dizziness, diaphoresis, flushing, hyperthermia), neuromuscular symptoms (e.g., tremor, rigidity, myoclonus, hyperreflexia, incoordination), seizures, and/or gastrointestinal symptoms (e.g., nausea, vomiting, diarrhea).

Concomitant use of dextroamphetamine saccharate, amphetamine aspartate, dextroamphetamine sulfate, amphetamine sulfate with MAOI drugs is contraindicated (see CONTRAINDICATIONS).

Discontinue treatment with dextroamphetamine saccharate, amphetamine aspartate, dextroamphetamine sulfate, amphetamine sulfate and any concomitant serotonergic agents immediately if the above symptoms occur, and initiate supportive symptomatic treatment. If concomitant use of dextroamphetamine saccharate, amphetamine aspartate, dextroamphetamine sulfate, amphetamine sulfate with other serotonergic drugs or CYP2D6 inhibitors is clinically warranted, initiate dextroamphetamine saccharate, amphetamine aspartate, dextroamphetamine sulfate, amphetamine sulfate with lower doses, monitor patients for the emergence of serotonin syndrome during drug initiation or titration, and inform patients of the increased risk for serotonin syndrome.

Visual Disturbance

Difficulties with accommodation and blurring of vision have been reported with stimulant treatment.

PRECAUTIONS

General

The least amount of amphetamine feasible should be prescribed or dispensed at one time in order to minimize the possibility of overdosage. Mixed salts of a single entity amphetamine product should be used with caution in patients who use other sympathomimetic drugs.

Tics

Amphetamines have been reported to exacerbate motor and phonic tics and Tourette’s syndrome. Therefore, clinical evaluation for tics and Tourette’s syndrome in children and their families should precede use of stimulant medications.

Information for Patients

Amphetamines may impair the ability of the patient to engage in potentially hazardous activities such as operating machinery or vehicles; the patient should therefore be cautioned accordingly.

Prescribers or other health professionals should inform patients, their families, and their caregivers about the benefits and risks associated with treatment with amphetamine or dextroamphetamine and should counsel them in its appropriate use. A patient medication guide is available for mixed salts of a single entity amphetamine product.

The prescriber or health professional should instruct patients, their families, and their caregivers to read the medication guide and should assist them in understanding its contents. Patients should be given the opportunity to discuss the contents of the medication guide and to obtain answers to any questions they may have. The complete text of the medication guide is reprinted at the end of this document.

Circulation Problems in Fingers and Toes [Peripheral Vasculopathy, Including Raynaud’s Phenomenon]

- Instruct patients beginning treatment with mixed salts of a single entity amphetamine product about the risk of peripheral vasculopathy, including Raynaud’s phenomenon, and associated signs and symptoms: fingers or toes may feel numb, cool, painful, and/or may change color from pale, to blue, to red.
- Instruct patients to report to their physician any new numbness, pain, skin color change, or sensitivity to temperature in fingers or toes.
- Instruct patients to call their physician immediately with any signs of unexplained wounds appearing on fingers or toes while taking mixed salts of a single entity amphetamine product.
- Further clinical evaluation (e.g., rheumatology referral) may be appropriate for certain patients.

Drug Interactions

Acidifying Agents

Lower blood levels and efficacy of amphetamines. Increase dose based on clinical response. Examples of acidifying agents include gastrointestinal acidifying agents (e.g., guanethidine, reserpine, glutamic acid HCl, ascorbic acid) and urinary acidifying agents (e.g., ammonium chloride, sodium acid phosphate, methenamine salts).

Adrenergic Blockers

Adrenergic blockers are inhibited by amphetamines.

Alkalinizing Agents

Increase blood levels and potentiate the action of amphetamine. Co-administration of mixed salts of a single entity amphetamine product and gastrointestinal alkalinizing agents should be avoided. Examples of alkalinizing agents include gastrointestinal alkalinizing agents (e.g., sodium bicarbonate) and urinary alkalinizing agents (e.g. acetazolamide, some thiazides).

Tricyclic Antidepressants

May enhance the activity of tricyclic or sympathomimetic agents causing striking and sustained increases in the concentration of d-amphetamine in the brain; cardiovascular effects can be potentiated. Monitor frequently and adjust or use alternative therapy based on clinical response. Examples of tricyclic antidepressants include desipramine, protriptyline.

CYP2D6 Inhibitors

The concomitant use of dextroamphetamine saccharate, amphetamine aspartate, dextroamphetamine sulfate, amphetamine sulfate and CYP2D6 inhibitors may increase the exposure of dextroamphetamine saccharate, amphetamine aspartate, dextroamphetamine sulfate, amphetamine sulfate compared to the use of the drug alone and increase the risk of serotonin syndrome. Initiate with lower doses and monitor patients for signs and symptoms of serotonin syndrome particularly during dextroamphetamine saccharate, amphetamine aspartate, dextroamphetamine sulfate, amphetamine sulfate initiation and after a dosage increase. If serotonin syndrome occurs, discontinue dextroamphetamine saccharate, amphetamine aspartate, dextroamphetamine sulfate, amphetamine sulfate and the CYP2D6 inhibitor (see WARNINGS, OVERDOSAGE). Examples of CYP2D6 Inhibitors include paroxetine and fluoxetine (also serotonergic drugs), quinidine, ritonavir.

Serotonergic Drugs

The concomitant use of dextroamphetamine saccharate, amphetamine aspartate, dextroamphetamine sulfate, amphetamine sulfate and serotonergic drugs increases the risk of serotonin syndrome. Initiate with lower doses and monitor patients for signs and symptoms of serotonin syndrome, particularly during dextroamphetamine saccharate, amphetamine aspartate, dextroamphetamine sulfate, amphetamine sulfate initiation or dosage increase. If serotonin syndrome occurs, discontinue dextroamphetamine saccharate, amphetamine aspartate, dextroamphetamine sulfate, amphetamine sulfate and the concomitant serotonergic drug(s) (see WARNINGS and PRECAUTIONS). Examples of serotonergic drugs include selective serotonin reuptake inhibitors (SSRI), serotonin norepinephrine reuptake inhibitors (SNRI), triptans, tricyclic antidepressants, fentanyl, lithium, tramadol, tryptophan, buspirone, St. John’s Wort.

MAO Inhibitors

Concomitant use of MAOIs and CNS stimulants can cause hypertensive crisis. Potential outcomes include death, stroke, myocardial infarction, aortic dissection, ophthalmological complications, eclampsia, pulmonary edema, and renal failure. Do not administer Adderall® concomitantly or within 14 days after discontinuing MAOI (see CONTRAINDICATIONS and WARNINGS). Examples of MAOIs include selegiline, tranylcypromine, isocarboxazid, phenelzine, linezolid, methylene blue.

Antihistamines

Amphetamines may counteract the sedative effect of antihistamines.

Antihypertensives

Amphetamines may antagonize the hypotensive effects of antihypertensives.

Chlorpromazine

Chlorpromazine blocks dopamine and norepinephrine receptors, thus inhibiting the central stimulant effects of amphetamines, and can be used to treat amphetamine poisoning.

Ethosuximide

Amphetamines may delay intestinal absorption of ethosuximide.

Haloperidol

Haloperidol blocks dopamine receptors, thus inhibiting the central stimulant effects of amphetamines.

Lithium Carbonate

The anorectic and stimulatory effects of amphetamines may be inhibited by lithium carbonate.

Meperidine

Amphetamines potentiate the analgesic effect of meperidine.

Methenamine Therapy

Urinary excretion of amphetamines is increased, and efficacy is reduced, by acidifying agents used in methenamine therapy.

Norepinephrine

Amphetamines enhance the adrenergic effect of norepinephrine.

Phenobarbital

Amphetamines may delay intestinal absorption of phenobarbital; coadministration of phenobarbital may produce a synergistic anticonvulsant action.

Phenytoin

Amphetamines may delay intestinal absorption of phenytoin; coadministration of phenytoin may produce a synergistic anticonvulsant action.

Propoxyphene

In cases of propoxyphene overdosage, amphetamine CNS stimulation is potentiated and fatal convulsions can occur.

Proton Pump Inhibitors

Time to maximum concentration (Tmax) of amphetamine is decreased compared to when administered alone. Monitor patients for changes in clinical effect and adjust therapy based on clinical response. An example of a proton pump inhibitor is omeprazole.

Veratrum Alkaloids

Amphetamines inhibit the hypotensive effect of veratrum alkaloids.

Drug/Laboratory Test Interactions

Amphetamines can cause a significant elevation in plasma corticosteroid levels. This increase is greatest in the evening. Amphetamines may interfere with urinary steroid determinations.

Carcinogenesis/Mutagenesis and Impairment of Fertility

No evidence of carcinogenicity was found in studies in which d, l-amphetamine (enantiomer ratio of 1:1) was administered to mice and rats in the diet for 2 years at doses of up to 30 mg/kg/day in male mice, 19 mg/kg/day in female mice, and 5 mg/kg/day in male and female rats. These doses are approximately 2.4, 1.5 and 0.8 times, respectively, the maximum recommended human dose of 30 mg/day [child] on a mg/m^2 body surface area basis.

Amphetamine, in the enantiomer ratio present in mixed salts of a single entity amphetamine product (immediate-release)(d- to l- ratio of 3:1), was not clastogenic in the mouse bone marrow micronucleus test in vivo and was negative when tested in the E. coli component of the Ames test in vitro. d,l-Amphetamine (1:1 enantiomer ratio) has been reported to produce a positive response in the mouse bone marrow micronucleus test, an equivocal response in the Ames test, and negative responses in the in vitro sister chromatid exchange and chromosomal aberration assays.

Amphetamine, in the enantiomer ratio present in mixed salts of a single entity amphetamine product (immediate-release)(d- to l- ratio of 3:1), did not adversely affect fertility or early embryonic development in the rat at doses of up to 20 mg/kg/day (approximately 5 times the maximum recommended human dose of 30 mg/day on a mg/m^2 body surface area basis).

Pregnancy

Teratogenic Effects

Amphetamine, in the enantiomer ratio present in mixed salts of a single entity amphetamine product (d- to l- ratio of 3:1), had no apparent effects on embryofetal morphological development or survival when orally administered to pregnant rats and rabbits throughout the period of organogenesis at doses of up to 6 mg/kg/day and 16 mg/kg/day, respectively. These doses are approximately 1.5 and 8 times, respectively, the maximum recommended human dose of 30 mg/day [child] on a mg/m^2 body surface area basis. Fetal malformations and death have been reported in mice following parenteral administration of d-amphetamine doses of 50 mg/kg/day (approximately 6 times that of a human dose of 30 mg/day [child] on a mg/m^2 basis) or greater to pregnant animals. Administration of these doses was also associated with severe maternal toxicity.

A number of studies in rodents indicate that prenatal or early postnatal exposure to amphetamine (d- or d,l-), at doses similar to those used clinically, can result in long-term neurochemical and behavioral alterations. Reported behavioral effects include learning and memory deficits, altered locomotor activity, and changes in sexual function.

There are no adequate and well-controlled studies in pregnant women. There has been one report of severe congenital bony deformity, tracheo-esophageal fistula, and anal atresia (vater association) in a baby born to a woman who took dextroamphetamine sulfate with lovastatin during the first trimester of pregnancy. Amphetamines should be used during pregnancy only if the potential benefit justifies the potential risk to the fetus.

Nonteratogenic Effects

Infants born to mothers dependent on amphetamines have an increased risk of premature delivery and low birth weight. Also, these infants may experience symptoms of withdrawal as demonstrated by dysphoria, including agitation, and significant lassitude.

Usage in Nursing Mothers

Amphetamines are excreted in human milk. Mothers taking amphetamines should be advised to refrain from nursing.

Pediatric Use

Long-term effects of amphetamines in children have not been well established. Amphetamines are not recommended for use in children under 3 years of age with attention deficit hyperactivity disorder described under INDICATIONS AND USAGE.

Geriatric Use

Mixed salts of a single entity amphetamine product have not been studied in the geriatric population.

ADVERSE REACTIONS

Cardiovascular

Palpitations, tachycardia, elevation of blood pressure, sudden death, myocardial infarction. There have been isolated reports of cardiomyopathy associated with chronic amphetamine use.

Central Nervous System

Psychotic episodes at recommended doses, overstimulation, restlessness, irritability, euphoria, dyskinesia, dysphoria, depression, tremor, tics, aggression, anger, logorrhea, dermatillomania.

Eye Disorders

Vision blurred, mydriasis.

Gastrointestinal

Dryness of the mouth, unpleasant taste, diarrhea, constipation, intestinal ischemia and other gastrointestinal disturbances. Anorexia and weight loss may occur as undesirable effects.

Allergic

Urticaria, rash, hypersensitivity reactions including angioedema and anaphylaxis. Serious skin rashes, including Stevens-Johnson syndrome and toxic epidermal necrolysis have been reported.

Endocrine

Impotence, changes in libido, frequent or prolonged erections.

Skin

Alopecia.

Musculoskeletal

Rhabdomyolysis.

To report SUSPECTED ADVERSE REACTIONS, contact Sandoz Inc. at 1-800-525-8747 or FDA at 1-800-FDA-1088 or www.fda.gov/medwatch.

DRUG ABUSE AND DEPENDENCE

Mixed salts of a single entity amphetamine product is a schedule II controlled substance.

Amphetamines have been extensively abused. Tolerance, extreme psychological dependence, and severe social disability have occurred. There are reports of patients who have increased the dosage to levels many times higher than recommended. Abrupt cessation following prolonged high dosage administration results in extreme fatigue and mental depression; changes are also noted on the sleep EEG. Manifestations of chronic intoxication with amphetamines include severe dermatoses, marked insomnia, irritability, hyperactivity, and personality changes. The most severe manifestation of chronic intoxication is psychosis, often clinically indistinguishable from schizophrenia.

OVERDOSAGE

Manifestations of amphetamine overdose include restlessness, tremor, hyperreflexia, rapid respiration, confusion, assaultiveness, hallucinations, panic states, hyperpyrexia and rhabdomyolysis. Fatigue and depression usually follow the central nervous system stimulation. Serotonin syndrome has also been reported. Cardiovascular effects include arrhythmias, hypertension or hypotension and circulatory collapse. Gastrointestinal symptoms include nausea, vomiting, diarrhea and abdominal cramps. Fatal poisoning is usually preceded by convulsions and coma.

Treatment

Consult with a certified poison control center for up to date guidance and advice.

DOSAGE AND ADMINISTRATION

Regardless of indication, amphetamines should be administered at the lowest effective dosage, and dosage should be individually adjusted according to the therapeutic needs and response of the patient. Late evening doses should be avoided because of the resulting insomnia.

Attention Deficit Hyperactivity Disorder

Not recommended for children under 3 years of age. In children from 3 to 5 years of age, start with 2.5 mg daily; daily dosage may be raised in increments of 2.5 mg at weekly intervals until optimal response is obtained.

In children 6 years of age and older, start with 5 mg once or twice daily; daily dosage may be raised in increments of 5 mg at weekly intervals until optimal response is obtained. Only in rare cases will it be necessary to exceed a total of 40 mg per day. Give first dose on awakening; additional doses (1 or 2) at intervals of 4 to 6 hours.

Where possible, drug administration should be interrupted occasionally to determine if there is a recurrence of behavioral symptoms sufficient to require continued therapy.

Narcolepsy

Usual dose 5 mg to 60 mg per day in divided doses, depending on the individual patient response.

Narcolepsy seldom occurs in children under 12 years of age; however, when it does, dextroamphetamine sulfate may be used. The suggested initial dose for patients aged 6 to 12 is 5 mg daily; daily dose may be raised in increments of 5 mg at weekly intervals until optimal response is obtained. In patients 12 years of age and older, start with 10 mg daily; daily dosage may be raised in increments of 10 mg at weekly intervals until optimal response is obtained. If bothersome adverse reactions appear (e.g., insomnia or anorexia), dosage should be reduced. Give first dose on awakening; additional doses (1 or 2) at intervals of 4 to 6 hours.

HOW SUPPLIED

Dextroamphetamine saccharate, amphetamine aspartate, dextroamphetamine sulfate and amphetamine sulfate tablets (Mixed salts of a single entity amphetamine product), for oral administration, are available as:

30 mg

Dark orange, round, biconvex tablets, debossed “E” over “404” on one side and double-bisected on the other side and supplied as:

- NDC: 71335-2070-1: 60 Tablets in a BOTTLE
- NDC: 71335-2070-2: 90 Tablets in a BOTTLE
- NDC: 71335-2070-3: 30 Tablets in a BOTTLE

Dispense contents in a tight, light-resistant container as defined in the USP with a child-resistant closure, as required. Protect from light and moisture. Keep tightly closed.

Store at 20°C to 25°C (68°F to 77°F) (See USP Controlled Room Temperature).

KEEP OUT OF THE REACH OF CHILDREN.

Repackaged/Relabeled by:
Bryant Ranch Prepack, Inc.
Burbank, CA 91504

MEDICATION GUIDE

Dextroamphetamine Saccharate, Amphetamine Aspartate,

Dextroamphetamine Sulfate and Amphetamine Sulfate Tablets CII

(Mixed Salts of a Single Entity Amphetamine Product)

(dex-troe-am-FET-ah-meen)

Rx Only

Read the medication guide that comes with mixed salts of a single entity amphetamine product before you or your child starts taking it and each time you get a refill. There may be new information. This medication guide does not take the place of talking to your doctor about you or your child’s treatment with mixed salts of a single entity amphetamine product.

BOXED WARNING

What is the most important information I should know about mixed salts of a single entity amphetamine product?

The following have been reported with use of mixed salts of a single entity amphetamine product and other stimulant medicines.

1. Heart-Related Problems:

• sudden death in patients who have heart problems or heart defects

• stroke and heart attack in adults

• increased blood pressure and heart rate

Tell your doctor if you or your child have any heart problems, heart defects, high blood pressure, or a family history of these problems.

Your doctor should check you or your child carefully for heart problems before starting mixed salts of a single entity amphetamine product.

Your doctor should check your or your child’s blood pressure and heart rate regularly during treatment with mixed salts of a single entity amphetamine product.

Call your doctor right away if you or your child have any signs of heart problems such as chest pain, shortness of breath, or fainting while taking mixed salts of a single entity amphetamine product.

2. Mental (Psychiatric) Problems:

All Patients

• new or worse behavior and thought problems

• new or worse bipolar illness

• new or worse aggressive behavior or hostility

Children and Teenagers

• new psychotic symptoms (such as hearing voices, believing things that are not true, are suspicious) or new manic symptoms

Tell your doctor about any mental problems you or your child have, or about a family history of suicide, bipolar illness, or depression.

Call your doctor right away if you or your child have any new or worsening mental symptoms or problems while taking mixed salts of a single entity amphetamine product, especially seeing or hearing things that are not real, believing things that are not real, or are suspicious.

3. Circulation Problems in Fingers and Toes [Peripheral Vasculopathy, Including Raynaud’s Phenomenon]:

- Fingers or toes may feel numb, cool, painful and/or may change color from pale, to blue, to red

Tell your doctor if you have or your child has numbness, pain, skin color change, or sensitivity to temperature in the fingers or toes.

Call your doctor right away if you have or your child has any signs of unexplained wounds appearing on fingers or toes while taking mixed salts of a single entity amphetamine product.

What are mixed salts of a single entity amphetamine product?

Mixed salts of a single entity amphetamine product are a central nervous system stimulant prescription medicine. It is used for the treatment of attention-deficit hyperactivity disorder (ADHD). Mixed salts of a single entity amphetamine product may help increase attention and decrease impulsiveness and hyperactivity in patients with ADHD.

Mixed salts of a single entity amphetamine product should be used as a part of a total treatment program for ADHD that may include counseling or other therapies.

Mixed salts of a single entity amphetamine product are also used in the treatment of a sleep disorder called narcolepsy.

Mixed salts of a single entity amphetamine product are a federally controlled substance (CII) because it can be abused or lead to dependence. Keep mixed salts of a single entity amphetamine product in a safe place to prevent misuse and abuse. Selling or giving away mixed salts of a single entity amphetamine product may harm others, and is against the law.

Tell your doctor if you or your child have (or have a family history of) ever abused or been dependent on alcohol, prescription medicines or street drugs.

Who should not take mixed salts of a single entity amphetamine product?

Mixed salts of a single entity amphetamine product should not be taken if you or your child:

• have heart disease or hardening of the arteries

• have moderate to severe high blood pressure

• have hyperthyroidism

• have an eye problem called glaucoma

• are very anxious, tense, or agitated

• have a history of drug abuse

• are taking or have taken within the past 14 days an anti-depression medicine called a monoamine oxidase inhibitor or MAOI

• are sensitive to, allergic to, or had a reaction to other stimulant medicines

Mixed salts of a single entity amphetamine product are not recommended for use in children less than 3 years old.

Mixed salts of a single entity amphetamine product may not be right for you or your child. Before starting mixed salts of a single entity amphetamine product tell your or your child’s doctor about all health conditions (or a family history of) including:

- heart problems, heart defects, high blood pressure
- mental problems including psychosis, mania, bipolar illness, or depression
- tics or Tourette’s syndrome
- liver or kidney problems
- thyroid problems
- seizures or have had an abnormal brain wave test (EEG)
- circulation problems in fingers or toes

Tell your doctor if you or your child are pregnant, planning to become pregnant, or breastfeeding.

Can mixed salts of a single entity amphetamine product be taken with other medicines?

Tell your doctor about all of the medicines that you or your child take including prescription and nonprescription medicines, vitamins, and herbal supplements. Mixed salts of a single entity amphetamine product and some medicines may interact with each other and cause serious side effects. Sometimes the doses of other medicines will need to be adjusted while taking mixed salts of a single entity amphetamine product.

Your doctor will decide whether mixed salts of a single entity amphetamine product can be taken with other medicines.

Especially tell your doctor if you or your child take:

- anti-depression medicines including MAOIs
- blood pressure medicines
- seizure medicines
- blood thinner medicines
- cold or allergy medicines that contain decongestants
- stomach acid medicines

Know the medicines that you or your child take. Keep a list of your medicines with you to show your doctor and pharmacist.

Do not start any new medicine while taking mixed salts of a single entity amphetamine product without talking to your doctor first.

How should mixed salts of a single entity amphetamine product be taken?

- Take mixed salts of a single entity amphetamine product exactly as prescribed. Your doctor may adjust the dose until it is right for you or your child.
- Mixed salts of a single entity amphetamine product are usually taken two to three times a day. The first dose is usually taken when you first wake in the morning. One or two more doses may be taken during the day, 4 to 6 hours apart.
- Mixed salts of a single entity amphetamine product can be taken with or without food.
- From time to time, your doctor may stop mixed salts of a single entity amphetamine product treatment for a while to check ADHD symptoms.
- Your doctor may do regular checks of the blood, heart, and blood pressure while taking mixed salts of a single entity amphetamine product. Children should have their height and weight checked often while taking mixed salts of a single entity amphetamine product. Mixed salts of a single entity amphetamine product treatment may be stopped if a problem is found during these check-ups.
- If you or your child take too much mixed salts of a single entity amphetamine product or overdoses, call your doctor or poison control center right away, or get emergency treatment.

What are possible side effects of mixed salts of a single entity amphetamine product?

See “What is the most important information I should know about mixed salts of a single entity amphetamine product?” for information on reported heart and mental problems.

Other serious side effects include:

- slowing of growth (height and weight) in children
- seizures, mainly in patients with a history of seizures
- eyesight changes or blurred vision
- Serotonin syndrome. A potentially life-threatening problem called serotonin syndrome can happen when medicines such as mixed salts of a single entity amphetamine product are taken with certain other medicines. Symptoms of serotonin syndrome may include:
  - agitation, hallucinations, coma or other changes in mental status
  - problems controlling your movements or muscle twitching
  - fast heartbeat
  - high or low blood pressure
  - sweating or fever
  - nausea or vomiting
  - diarrhea
  - muscle stiffness or tightness

Common side effects include:

- stomach ache
- decreased appetite
- nervousness

Mixed salts of a single entity amphetamine product may affect you or your child’s ability to drive or do other dangerous activities.

Talk to your doctor if you or your child have side effects that are bothersome or do not go away.

This is not a complete list of possible side effects. Ask your doctor or pharmacist for more information.

Call your doctor for medical advice about side effects. You may report side effects to FDA at 1-800-FDA-1088.

How should I store mixed salts of a single entity amphetamine product?

- Store mixed salts of a single entity amphetamine product in a safe place at room temperature, 20° to 25° C (68° to 77° F).
- Keep mixed salts of a single entity amphetamine product and all medicines out of the reach of children.

General information about mixed salts of a single entity amphetamine product.

Medicines are sometimes prescribed for purposes other than those listed in a medication guide. Do not use mixed salts of a single entity amphetamine product for a condition for which it was not prescribed. Do not give mixed salts of a single entity amphetamine product to other people, even if they have the same condition. It may harm them and it is against the law.

This medication guide summarizes the most important information about mixed salts of a single entity amphetamine product. If you would like more information, talk with your doctor. You can ask your doctor or pharmacist for information about mixed salts of a single entity amphetamine product that was written for healthcare professionals. For more information about mixed salts of a single entity amphetamine product, please contact Sandoz Inc. at 1-800-525-8747.

What are the ingredients in mixed salts of a single entity amphetamine product?

Active Ingredients: dextroamphetamine saccharate, amphetamine aspartate monohydrate, dextroamphetamine sulfate USP, amphetamine sulfate USP

Inactive Ingredients: lactose monohydrate, pregelatinized starch (corn) and magnesium stearate.

In addition the 5 mg and 10 mg tablets contain FD&C blue No. 1 aluminum lake and the 20 mg and 30 mg tablets contain FD&C yellow No. 6 aluminum lake as color additives.

KEEP OUT OF THE REACH OF CHILDREN.

This Medication Guide has been approved by the U.S. Food and Drug Administration.

Manufactured by

Sandoz Inc., Princeton, NJ 08540

46299645

Rev. Mar 2022

MF42031850REV03/22

PACKAGE LABEL

Dextroamphetamine Saccharate, Amphetamine Aspartate,

Dextroamphetamine Sulfate and Amphetamine Sulfate Tablets

(Mixed Salts of A Single Entity Amphetamine Product) 30 mg (CII)